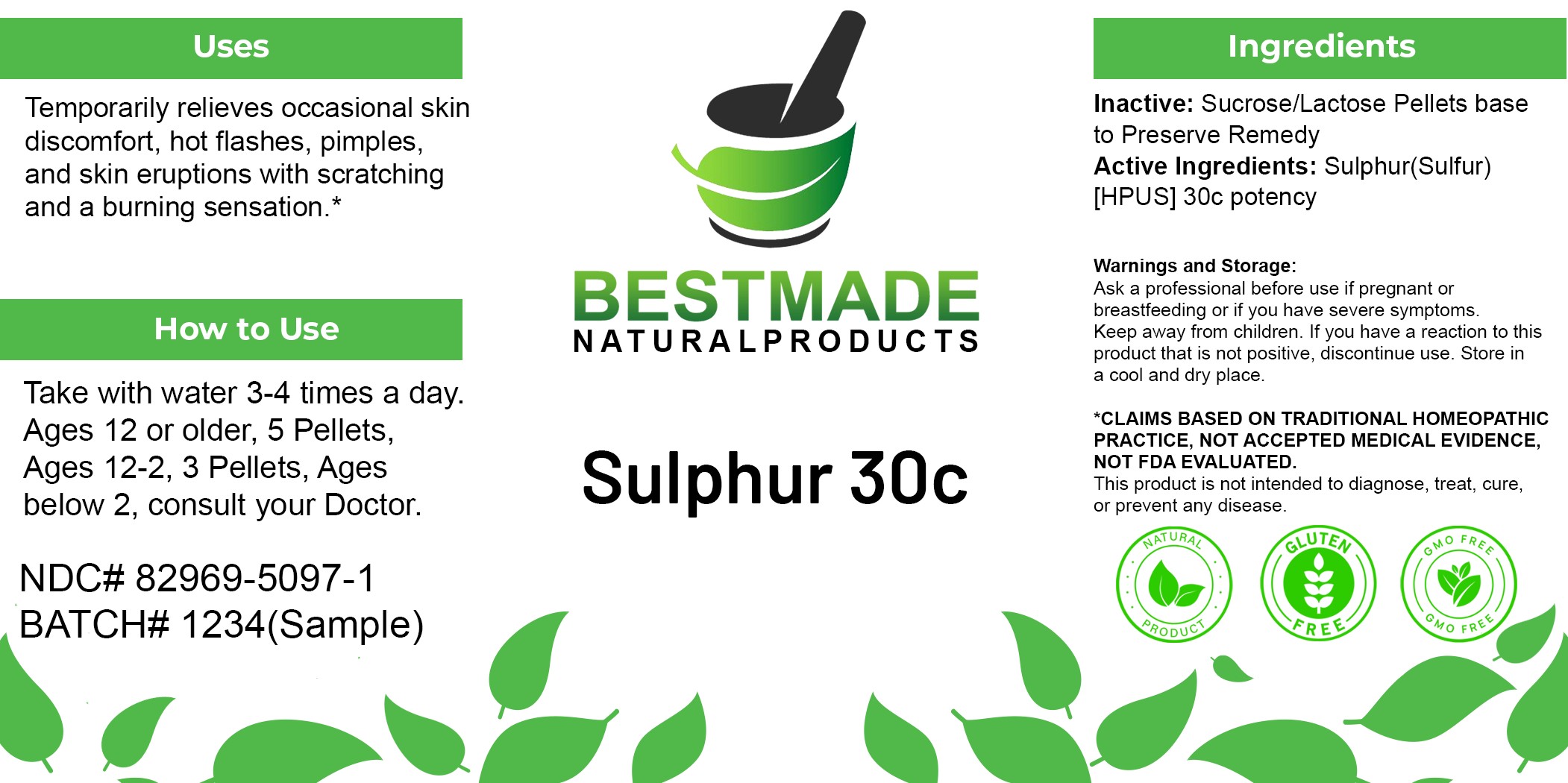 DRUG LABEL: Bestmade Natural Products Sulphur
NDC: 82969-5097 | Form: TABLET, SOLUBLE
Manufacturer: Bestmade Natural Products
Category: homeopathic | Type: HUMAN OTC DRUG LABEL
Date: 20250527

ACTIVE INGREDIENTS: SULFUR 30 [hp_C]/30 [hp_C]
INACTIVE INGREDIENTS: LACTOSE, UNSPECIFIED FORM 30 [hp_C]/30 [hp_C]; SUCROSE 30 [hp_C]/30 [hp_C]

Sulphur 30c

DOSAGE AND ADMINISTRATION

How to Use

Take with water 3-4 times a day. Ages 12 or older, 5 Pellets, Ages 12-2, 3 Pellets, Ages below 2, consult your Doctor.

INDICATIONS AND USAGE

Best for

Temporarily relieves occasional skin discomfort, hot flashes, pimples, and skin eruptions with scratching and a burning sensation.*

INACTIVE INGREDIENT

Ingredients

Inactive: Sucrose/Lactose Pellets base to Preserve Remedy

Active Ingredients: Sulphur(Sulfur) [HPUS] 30c potency

Warnings:

Ask a professional before use if pregnant or breastfeeding or if you have severe symptoms.

Keep away from children. If you have a reaction to this product that is not positive, discontinue use. Store in a cool and dry place

*CLAIMS BASED ON TRADITIONAL HOMEOPATHIC PRACTICE, NOT ACCEPTED MEDICAL EVIDENCE NOT FDA EVALUATED.
This product is not intended to diagnose, treat, cure, or prevent any disease.

PURPOSE

Best for

Temporarily relieves occasional skin discomfort, hot flashes, pimples, and skin eruptions with scratching and a burning sensation.*

Warnings:

Ask a professional before use if pregnant or breastfeeding or if you have severe symptoms.

Keep away from children. If you have a reaction to this product that is not positive, discontinue use. Store in a cool and dry place

*CLAIMS BASED ON TRADITIONAL HOMEOPATHIC PRACTICE, NOT ACCEPTED MEDICAL EVIDENCE NOT FDA EVALUATED.
This product is not intended to diagnose, treat, cure, or prevent any disease.

Entire package label